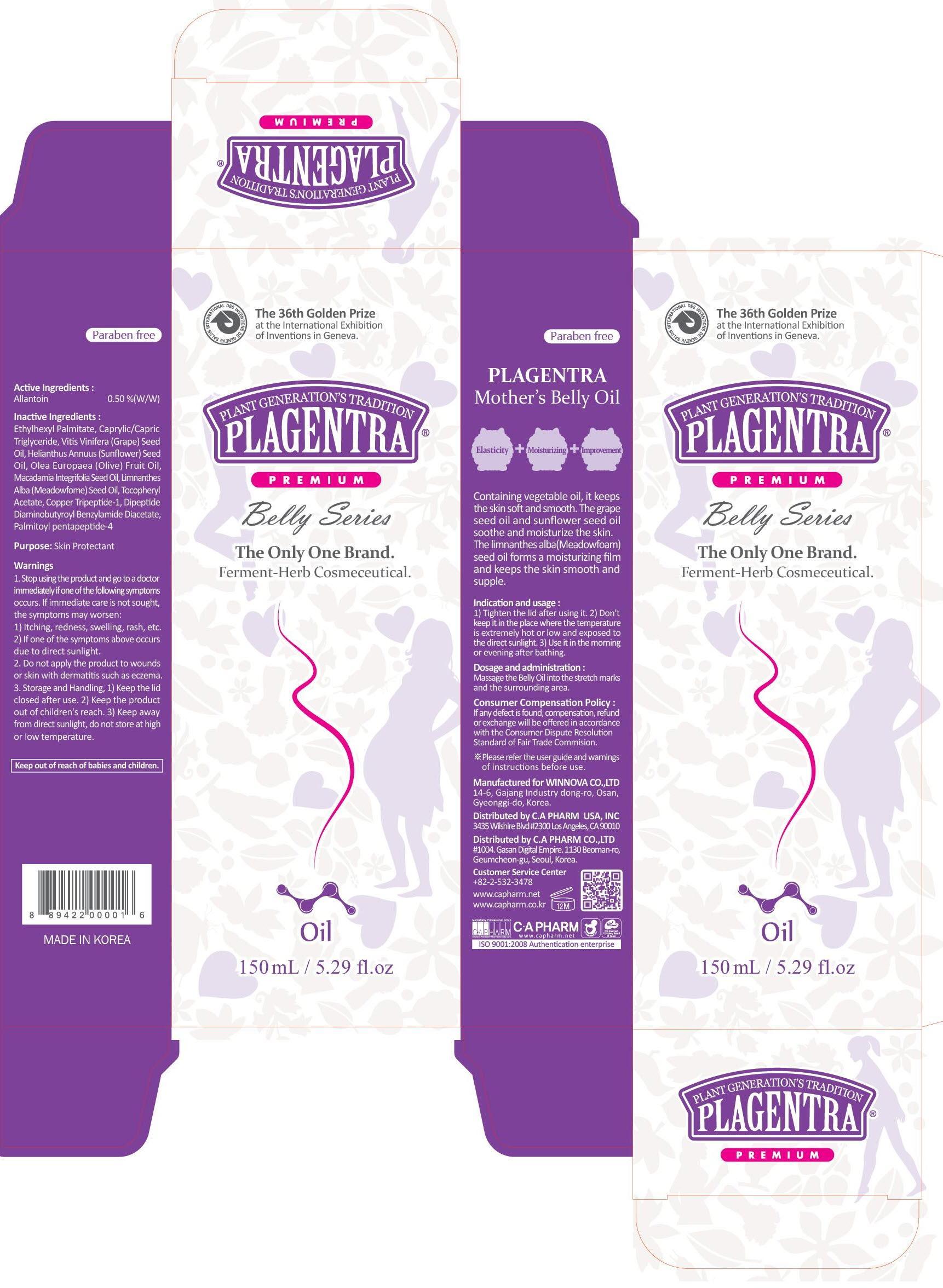 DRUG LABEL: PLAGENTRA MOTHERS BELLY
NDC: 68988-030 | Form: OIL
Manufacturer: C.A Pharm Co., Ltd.
Category: otc | Type: HUMAN OTC DRUG LABEL
Date: 20141205

ACTIVE INGREDIENTS: Allantoin 0.75 mg/150 mL
INACTIVE INGREDIENTS: Ethylhexyl Palmitate; GRAPE SEED OIL

ACTIVE INGREDIENT

Active Ingredient: Allantoin 0.5%

INACTIVE INGREDIENT

Inactive Ingredients:
Ethylhexyl Palmitate, Caprylic/Capric Triglyceride, Vitis Vinifera (Grape) Seed Oil, Helianthus Annuus (Sunflower) Seed Oil, Olea Europaea (Olive) Fruit Oil, Macadamia Integrifolia Seed Oil, Limnanthes Alba (Meadowfome) Seed Oil, Tocopheryl Acetate, Copper Tripeptide-1, Dipeptide Diaminobutyroyl Benzylamide Diacetate, Palmitoyl pentapeptide-4

PURPOSE

Purpose: Skin Protectant

WARNINGS

1. Stop using the product and go to a doctor immediately if one of the following symptoms occurs. If immediate care is not sought, the symptoms may worsen :
1) Itching, redness, swelling, rash, etc. 2) If one of the symptoms above occurs due to direct sunlight.
2. Do not apply the product to wounds or skin with dermatitis such as eczema.
3. Storage and Handling, 1) Keep the lid closed after use. 2) Keep the product out of children's reach. 3) Keep away from direct sunlight, do not store at high or low temperature.

KEEP OUT OF REACH OF CHILDREN

keep out of reach of babies and children.

INDICATIONS & USAGE

Indication and usage:
1) Tighten the lid after using it. 2) Don't keep it in the place where the temperature is extremely hot or low and exposed to the direct sunlight. 3) Use it in the morning or evening after shower.

DOSAGE & ADMINISTRATION

Dosage and administration:
Massage the Belly Oil into the stretch marks and the surrounding area.